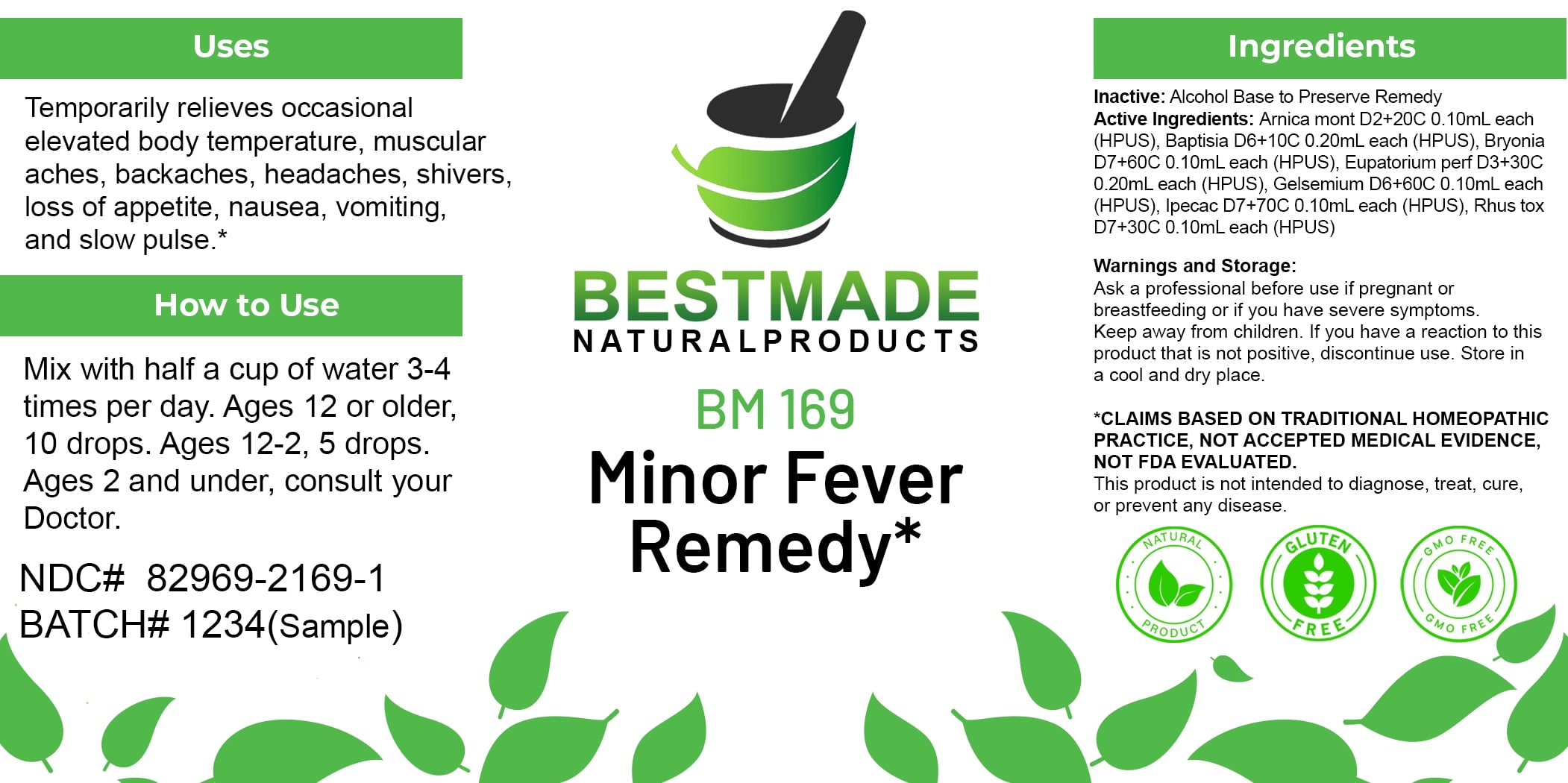 DRUG LABEL: Bestmade Natural Products BM169
NDC: 82969-2169 | Form: LIQUID
Manufacturer: Bestmade Natural Products
Category: homeopathic | Type: HUMAN OTC DRUG LABEL
Date: 20250219

ACTIVE INGREDIENTS: TOXICODENDRON PUBESCENS LEAF 30 [hp_C]/30 [hp_C]; ARNICA MONTANA 30 [hp_C]/30 [hp_C]; IPECAC 30 [hp_C]/30 [hp_C]; EUPATORIUM PERFOLIATUM FLOWERING TOP 30 [hp_C]/30 [hp_C]; GELSEMIUM SEMPERVIRENS ROOT 30 [hp_C]/30 [hp_C]; BRYONIA ALBA ROOT 30 [hp_C]/30 [hp_C]; BAPTISIA TINCTORIA ROOT 30 [hp_C]/30 [hp_C]
INACTIVE INGREDIENTS: ALCOHOL 30 [hp_C]/30 [hp_C]

BM169

DOSAGE AND ADMINISTRATION

How to Use

Mix with half a cup of water 3-4 times per day. Ages 12 or older, 10 drops. Ages 12-2, 5 drops. Ages 2 and under, consult your Doctor.

INACTIVE INGREDIENT

Ingredients

Inactive: Alcohol Base to Preserve Remedy

ACTIVE INGREDIENT

Active Ingredients: Arnica mont D2+20C 0.10ml each (HPUS), Baptisia D6+10C 0.20ml each (HPUS), Bryonia D7+80C 0.10ml each (HPUS), Eupatorium perf D3+30C 0.20ml each (HPUS), Gelsemium D6+60C 0.10ml each (HPUS), Ipecac D7+70C 0.10ml each (HPUS), Rhus tox D7+30C 0.10ml each (HPUS)

Uses

Temporarily relieves occasional elevated body temperature, muscular aches, backaches, headaches, shivers, loss of appetite, nausea, vomiting, and slow pulse.*

*CLAIMS BASED ON TRADITIONAL HOMEOPATHIC PRACTICE. NOT ACCEPTED MEDICAL EVIDENCE. NOT FDA EVALUATED.

This product is not intended to diagnose, treat, cure, or prevent any disease.

Uses

Temporarily relieves occasional elevated body temperature, muscular aches, backaches, headaches, shivers, loss of appetite, nausea, vomiting, and slow pulse.*

*CLAIMS BASED ON TRADITIONAL HOMEOPATHIC PRACTICE. NOT ACCEPTED MEDICAL EVIDENCE. NOT FDA EVALUATED.

This product is not intended to diagnose, treat, cure, or prevent any disease.

KEEP OUT OF REACH OF CHILDREN

Warnings and Storage:

Ask a professional before use if pregnant or breastfeeding or if you have severe symptoms. Keep away from children. If you have a reaction to this product that is not positive, discontinue use. Store in a cool and dry place.

Warnings and Storage:

Ask a professional before use if pregnant or breastfeeding or if you have severe symptoms. Keep away from children. If you have a reaction to this product that is not positive, discontinue use. Store in a cool and dry place.

*CLAIMS BASED ON TRADITIONAL HOMEOPATHIC PRACTICE, NOT ACCEPTED MEDICAL EVIDENCE NOT FDA EVALUATED.

This product is not intended to diagnose, treat, cure, or prevent any disease.

Entire package label